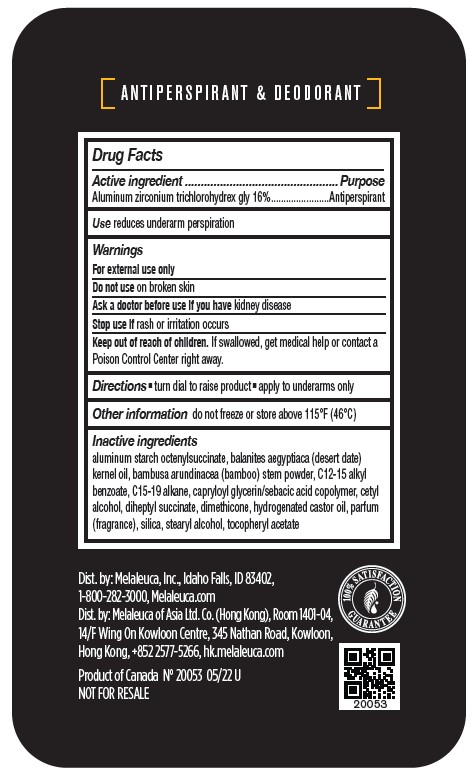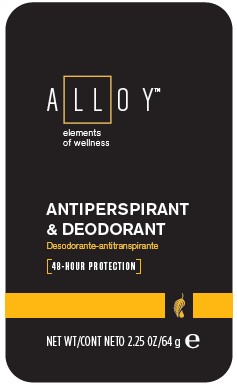 DRUG LABEL: Alloy
NDC: 54473-405 | Form: STICK
Manufacturer: Melaleuca, Inc
Category: otc | Type: HUMAN OTC DRUG LABEL
Date: 20250214

ACTIVE INGREDIENTS: ALUMINUM ZIRCONIUM TETRACHLOROHYDREX GLY 10.24 g/64 g
INACTIVE INGREDIENTS: CETYL ALCOHOL; DIMETHICONE; HYDROGENATED CASTOR OIL; STEARYL ALCOHOL; ALPHA-TOCOPHEROL ACETATE; BAMBUSA ARUNDINACEA STEM; C15-19 ALKANE; ALUMINUM STARCH OCTENYLSUCCINATE; PARFUMIDINE; CAPRYLOYL GLYCERIN/SEBACIC ACID COPOLYMER (2000 MPA.S); ALKYL (C12-15) BENZOATE; BALANITES AEGYPTIACA SEED OIL; DIHEPTYL SUCCINATE; SILICON DIOXIDE

Alloy Antiperspirant & Deodorant

Active ingredient
Aluminum zirconium tetrachlorohydrex-gly 16%

Purpose
Antiperspirant

INDICATIONS AND USAGE

Use reduces underarm perspiration

Warnings
For external use only

Do not use on broken skin

Ask a doctor before use if you have kidney disease

Stop use and ask a doctor if rash or irritation occurs

Keep out of reach of children. If swallowed, get medical help or contact a Poison Control Center right away.

Directions

- turn dial to raise product
- apply to underarms only

Other information do not freeze or store above 115°F (46°C)

Inactive ingredients
Aloe barbadensis leaf juice, Camellia sinensis leaf extract, cyclopentasiloxane, fragrance, hydrogenated castor oil, PEG-8 distearate, PPG-14 butyl ether, sodium bicarbonate, stearyl alcohol, talc, tocopherol, Zea mays (corn) starch